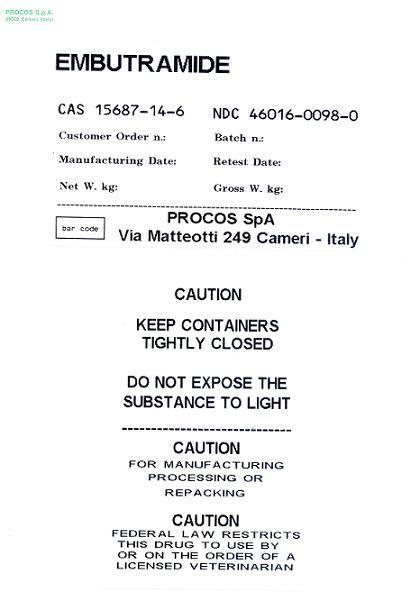 DRUG LABEL: Embutramide
NDC: 46016-0098 | Form: POWDER
Manufacturer: PROCOS S.p.A.
Category: other | Type: BULK INGREDIENT - ANIMAL DRUG
Date: 20211007
DEA Schedule: CIII

ACTIVE INGREDIENTS: EMBUTRAMIDE 50 kg/50 kg

Embutramide

PACKAGE LABEL

EMBUTRAMIDE

NDC 46016-0098-0

PROCOS SpA

Via Matteotti 249 Cameri - Italy

CAUTION

KEEP CONTAINERS TIGHTLY CLOSED

DO NOT EXPOSE THE SUBSTANCE TO LIGHT

CAUTION

FOR MANUFACTURING, PROCESSING OR REPACKING

CAUTION

FEDERAL LAW RESTRICTS THIS DRUG TO USE BY OR ON THE ORDER OF A LICENSED VETERINARIAN